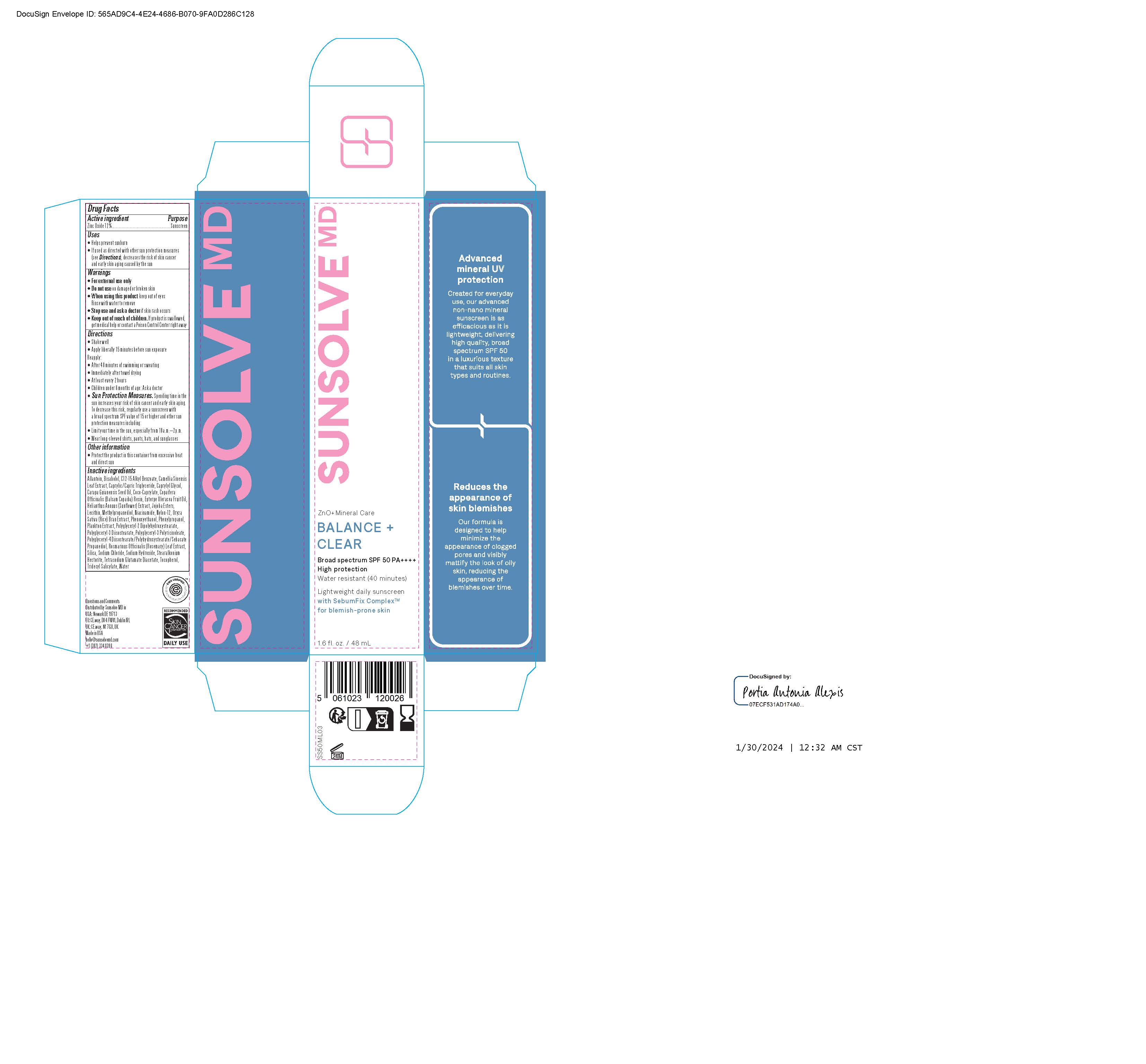 DRUG LABEL: Sunsolve MD Balance and Clear
NDC: 84878-997 | Form: LOTION
Manufacturer: Sunsolve MD Inc
Category: otc | Type: HUMAN OTC DRUG LABEL
Date: 20251114

ACTIVE INGREDIENTS: ZINC OXIDE 132 mg/1 mL
INACTIVE INGREDIENTS: CAMELLIA SINENSIS LEAF OIL; CAPRYLIC/CAPRIC TRIGLYCERIDE; EUTERPE OLERACEA FRUIT OIL; CARAPA GUIANENSIS SEED OIL; SILICON DIOXIDE; COPAIFERA OFFICINALIS (BALSAM COPAIBA) RESIN; PHENOXYETHANOL; JOJOBA OIL; ORYZA SATIVA WHOLE; TRIDECYL SALICYLATE; TOCOPHEROL; CAPRYLYL GLYCOL; COCO-CAPRYLATE; NYLON-12; PHENYLPROPANOL; HELIANTHUS ANNUUS FLOWERING TOP; LECITHIN, SOYBEAN; METHYLPROPANEDIOL; POLYGLYCERYL-2 DIPOLYHYDROXYSTEARATE; ALLANTOIN; ALKYL (C12-15) BENZOATE; ROSMARINUS OFFICINALIS FLOWER; .ALPHA.-BISABOLOL, (+)-; SODIUM HYDROXIDE; WATER; NIACINAMIDE; PROPANEDIOL; TETRASODIUM GLUTAMATE DIACETATE; SODIUM CHLORIDE; POLYGLYCERYL-4 DIISOSTEARATE/POLYHYDROXYSTEARATE/SEBACATE; POLYGLYCERYL-3 DIISOSTEARATE; STEARALKONIUM HECTORITE

Sunsolve MD Balance and Clear